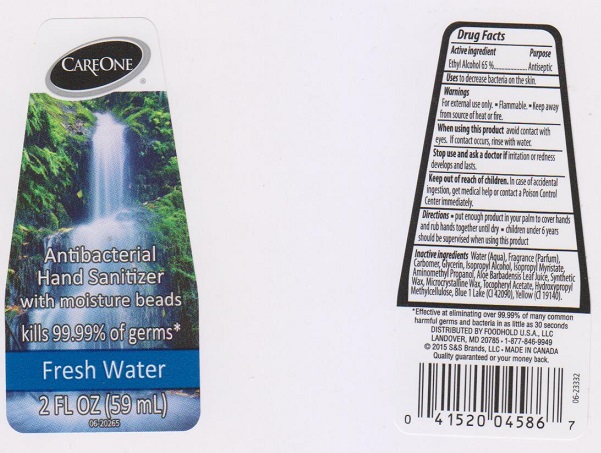 DRUG LABEL: CAREONE
NDC: 41520-412 | Form: LIQUID
Manufacturer: American Sales Company
Category: otc | Type: HUMAN OTC DRUG LABEL
Date: 20170426

ACTIVE INGREDIENTS: ALCOHOL 650 mg/1 mL
INACTIVE INGREDIENTS: WATER; CARBOMER 934; GLYCERIN; ISOPROPYL ALCOHOL; ISOPROPYL MYRISTATE; AMINOMETHYLPROPANOL; ALOE VERA LEAF; SYNTHETIC WAX (1800 MW); MICROCRYSTALLINE WAX; .ALPHA.-TOCOPHEROL ACETATE, DL-; HYPROMELLOSES; FD&C BLUE NO. 1; FD&C YELLOW NO. 5

Drug Facts

Active ingredient

Ethyl Alcohol 65%

Purpose

Antiseptic

Uses

to decrease bacteria on the skin.

Warnings

For external use only.

- Flammable
- Keep away from source of heat or fire

When using this product

avoid contact with eyes. If contact occurs, rinse with water.

Stop use and ask a doctor if

irritation or redness develops and lasts.

Keep out of reach of children.

In case of accidental ingestion, get medical help or contact a Poison Control Center immediately.

Directions

- put enough product in your palm to cover hands and rub hands together until dry.
- children under 6 years should be supervised when using this product

Inactive ingredients

Water (Aqua), Fragrance (Parfum), Carbomer, Glycerin, Isopropyl Alcohol, Isopropyl Myristate, Aminomethyl Propanol, Aloe Barbadensis Leaf Juice, Synthetic Wax, Microcrystalline Wax, Tocopheryl Acetate, Hydroxypropyl Methylcellulose, Blue 1 Lake (CI 42090), Yellow 5 (CI 19140).